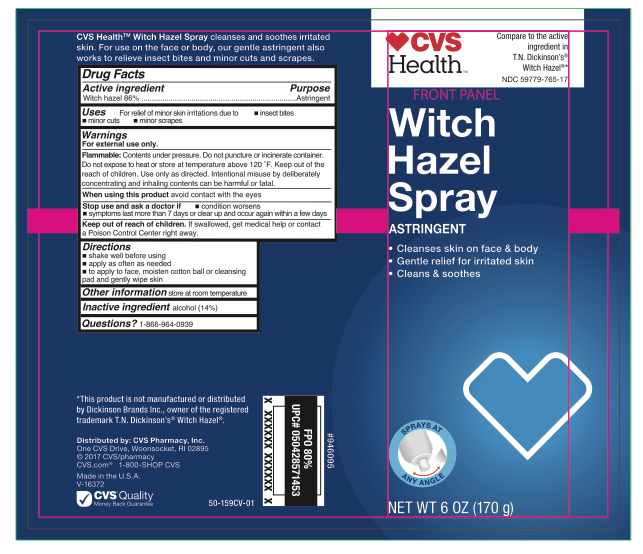 DRUG LABEL: Witch Hazel
NDC: 59779-765 | Form: SPRAY
Manufacturer: CVS Pharmacy
Category: otc | Type: HUMAN OTC DRUG LABEL
Date: 20241115

ACTIVE INGREDIENTS: WITCH HAZEL 146 g/170 g
INACTIVE INGREDIENTS: ALCOHOL

CVS Witch Hazel Spray

Active ingredient

Witch Hazel

Purpose

Astringent

Uses

For relief of minor skin irritation due to

- insect bites
- minor cuts
- minor scrapes

Warnings

For external use only.

Flammable:

Avoid spraying in eyes. Content under pressure. Do not puncture or incinerate. Do not store at temperatures above 120 oF. Keep out of reach of children. Use only as directede. Intentional misuse by deliberately concentrating and inhaling the contents can be harmful or fatal.

When using this product

avoid contact with the eyes. If contact occurs rince thoroughly with water.

Stop use and ask doctor of

- condition worsens
- symptoms last more than 7 days or clear up and occur again within a few days

Keep out of reach of children

If swallowed, get medical help or contact a Poison Control Center right away.

Directions

- apply as often as needed
- to apply to face, moisten cotton ball or cleansing pad and gently wipe skin

Other Information

Store at room temperature

Inactive Ingredients

Alcohol (14%)

Questions?

1-866-964-0939

Principal Display Panel

CVS Health

Witch Hazel Spray
Astringent

- Cleanses skin on face & body
- Gentle relief for irritated skin
- Cleans & soothes

NET WT 6 OZ (170 g)